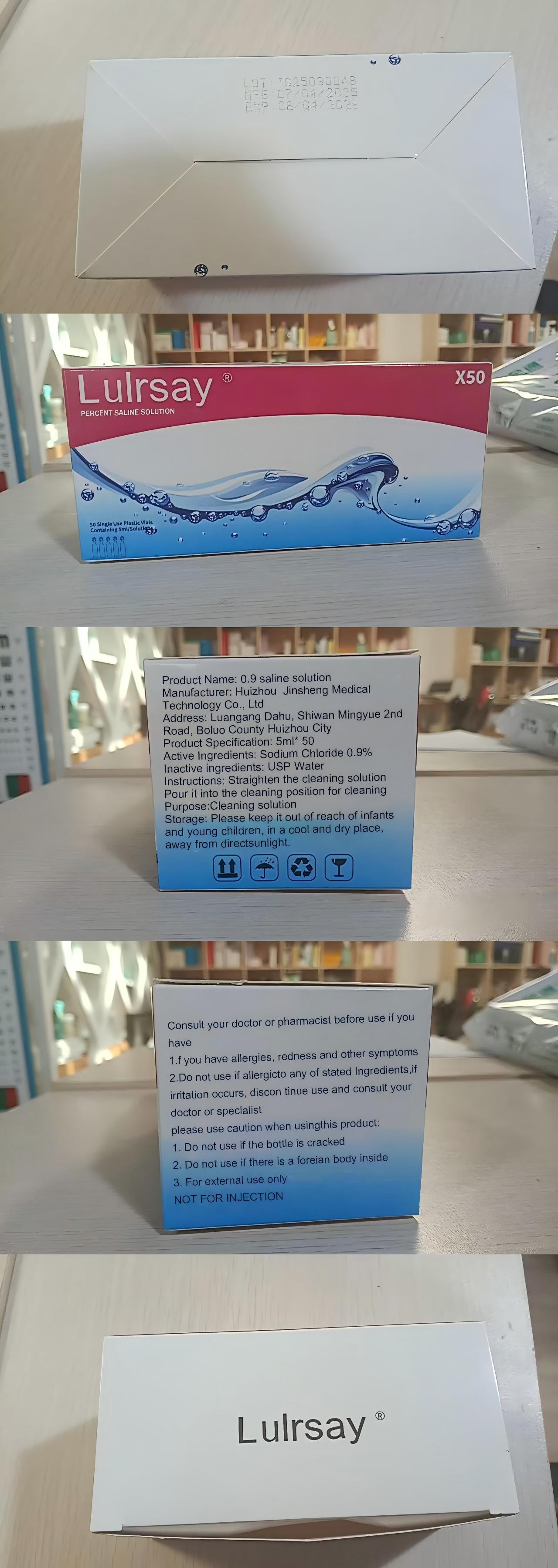 DRUG LABEL: 0.9saline
NDC: 87311-102 | Form: SOLUTION
Manufacturer: Huizhou Jinsheng Medical Technology Co., Ltd
Category: otc | Type: HUMAN OTC DRUG LABEL
Date: 20260203

ACTIVE INGREDIENTS: SODIUM CHLORIDE 9 mg/1 mL
INACTIVE INGREDIENTS: WATER

0.9 saline

PURPOSE

Cleaning solution

KEEP OUT OF REACH OF CHILDREN

Please keep it out of reach of infantsand young children, in a cool and dry place,away from direct sunlight.

INDICATIONS AND USAGE

Straighten the cleaning solution Pour it into the cleaning position for cleaning

WARNINGS

Consult your doctor or pharmacist before use if you have
1. If you have allergies, redness and other symptoms
2. Do not use if allergic to any of stated Ingredients,if irritation occurs, discontinue use and consult your doctor or specialist
please use caution when using this product:
1. Do not use if the bottle is cracked
2. Do not use if there is a foreign body inside
3. For external use only

NOT FOR INJECTION

Single use dosage vials 5ml each

Active ingredient: Sodium Chloride 0.9%

Inactive ingredient: USP Water

QUESTIONS

Manufacturer:

Huizhou Jinsheng Medical Technology Co., Ltd

Luangang Dahu, Shiwan Mingyue 2nd Road, Boluo County, Huizhou, Guangdong, China, 516000

See Label